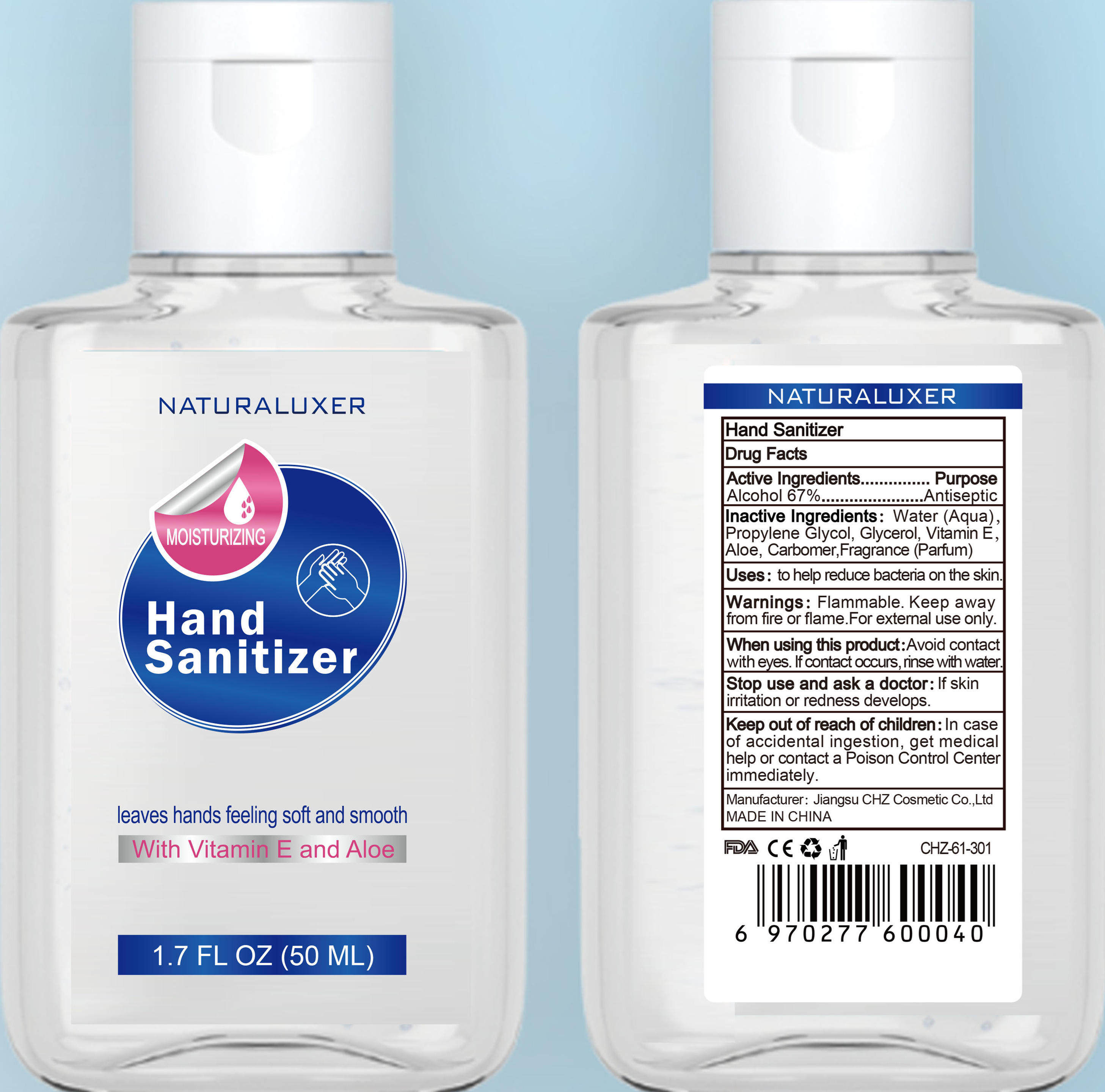 DRUG LABEL: Hand Sanitizer
NDC: 54283-001 | Form: LIQUID
Manufacturer: Jiangsu CHZ Cosmetic Co., Ltd.
Category: otc | Type: HUMAN OTC DRUG LABEL
Date: 20200411

ACTIVE INGREDIENTS: ALCOHOL 33.4 mL/50 mL
INACTIVE INGREDIENTS: GLYCERIN; ALOE; PROPYLENE GLYCOL; WATER

PURPOSE

leaves hands feling soft and smooth

ACTIVE INGREDIENT

Alcohol

INACTIVE INGREDIENT

Water（Aqua）

Glycerol

Propylene Glycol

Aloe

keep out of children

INDICATIONS AND USAGE

Smear palms,Wash your hands with water

WARNINGS

Flammable. Keep away from fre or flame.For extemal use only.When using this product:Avoid contact with eyes. If contact occurs, rinse withwater.Stop use and ask a doctor

DOSAGE AND ADMINISTRATION

Disinfection
Sterilization
No Rinseing